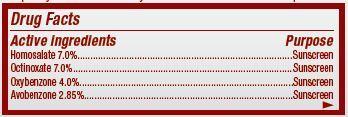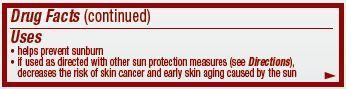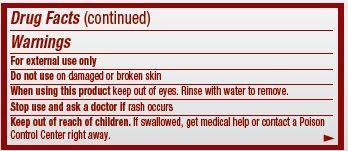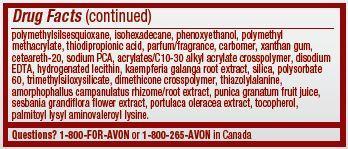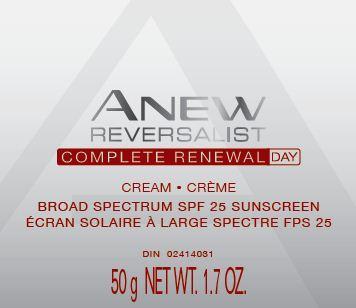 DRUG LABEL: Anew Reversalist
NDC: 10096-0312 | Form: CREAM
Manufacturer: New Avon LLC
Category: otc | Type: HUMAN OTC DRUG LABEL
Date: 20190101

ACTIVE INGREDIENTS: HOMOSALATE 70 mg/1 g; OCTINOXATE 70 mg/1 g; OXYBENZONE 40 mg/1 g; AVOBENZONE 28.5 mg/1 g
INACTIVE INGREDIENTS: WATER

Anew Reversalist Complete Renewal Day Cream Broad Spectrum SPF 25

Active ingredient
Homosalate 7.0%...............
Octinoxate 7.0%.................
Oxybenzone 4.0%...........
Avobenzone 2.85%..........

Purpose
.................................Sunscreen

.................................Sunscreen

.................................Sunscreen

.................................Sunscreen

Uses
• helps prevent sunburn

• if used as directed with other sun protection measures (see Directions), decreases the risk of skin cancer and early skin aging caused by the sun

Warnings
For external use only

Do not use on damaged or broken skin

When using this product keep out of eyes. Rinse with water to remove.

Stop use and ask a doctor if rash occurs

Keep out of reach of children. If swallowed, get medical help or contact a Poison Control Center right away.

Directions
• apply liberally 15 minutes before sun exposure
• children under 6 months of age: ask a doctor
• reapply at least every 2 hours
• use a water resistant sunscreen if swimming or sweating
• Sun Protection Measures. Spending time in the sun increases your risk of skin cancer and early skin aging. To decrease this risk, regularly use a sunscreen with a Broad Spectrum SPF value of 15 or higher and other sun protection measures including:
• limit time in the sun, especially from 10 a.m. – 2 p.m.
• wear long-sleeved shirts, pants, hats, and sunglasses

Other information

• protect the product in this container from excessive heat and direct sun

Inactive Ingredients:
water/eau, glycerin, dimethicone, butylene glycol, isodecyl isononanoate, tromethamine, dilauryl thiodipropionate, phytol, ethylhexylglycerin, hydroxyethyl acrylate/sodium acryloyldimethyl taurate copolymer, cetearyl alcohol, nylon-12, polymethylsilsesquioxane, isohexadecane, phenoxyethanol, polymethyl methacrylate, thiodipropionic acid, parfum/fragrance, carbomer, xanthan gum, ceteareth-20, sodium PCA, acrylates/C10-30 alkyl acrylate crosspolymer, disodium EDTA, hydrogenated lecithin, kaempferia galanga root extract, silica, polysorbate 60, trimethylsiloxysilicate, dimethicone crosspolymer, thiazolylalanine, amorphophallus campanulatus rhizome/root extract, punica granatum fruit juice, sesbania grandiflora flower extract, portulaca oleracea extract, tocopherol, palmitoyl lysyl aminovaleroyl lysine.

Questions?
1-800-FOR-AVON or 1-800-265-AVON in Canada